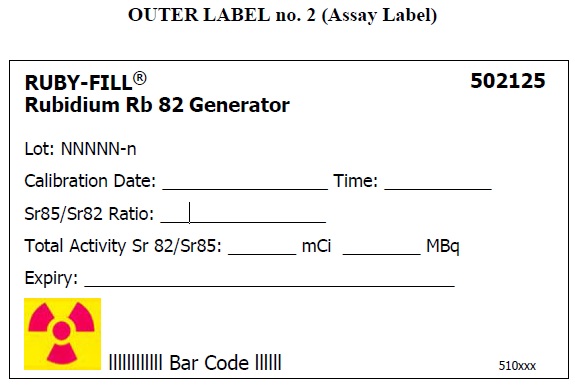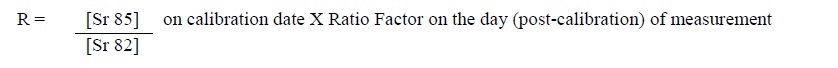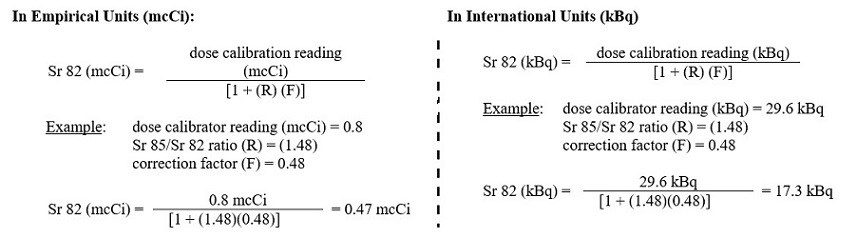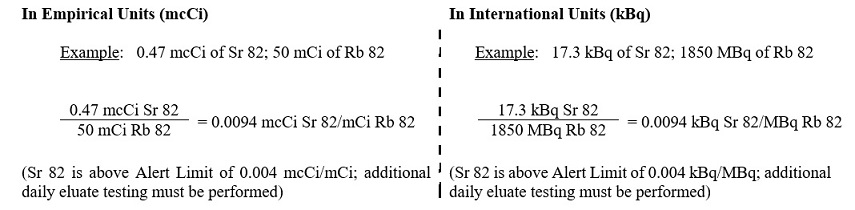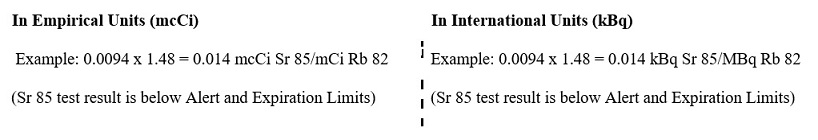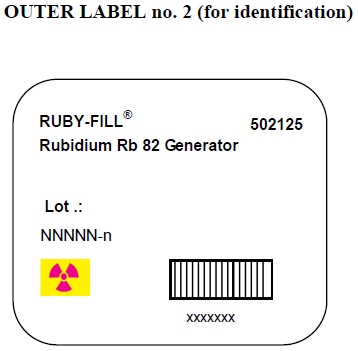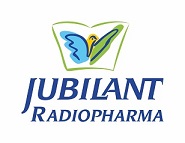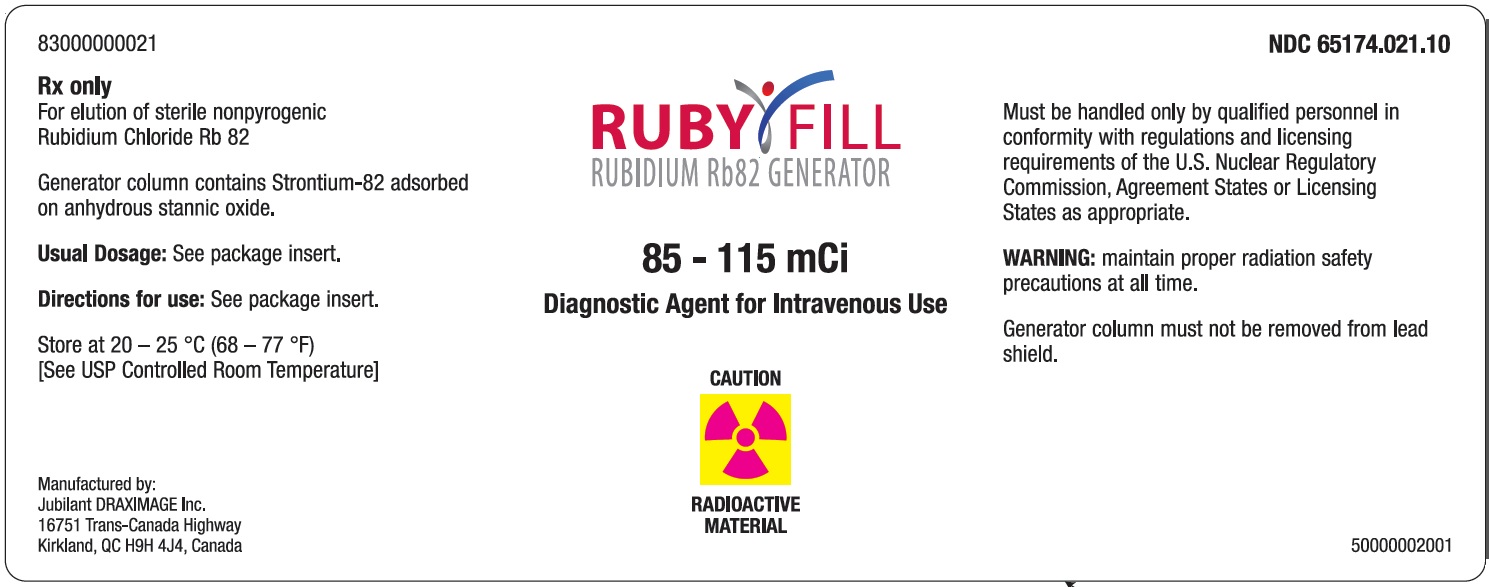 DRUG LABEL: 
                  RUBY-FILL
NDC: 65174-021 | Form: INJECTION, SOLUTION
Manufacturer: Jubilant DraxImage Inc., dba Jubilant Radiopharma
Category: prescription | Type: Human Prescription Drug Label
Date: 20201020

ACTIVE INGREDIENTS: RUBIDIUM CHLORIDE RB-82 100 mCi/1 1

HIGHLIGHTS OF PRESCRIBING INFORMATION

These highlights do not include all the information needed to use RUBY-FILL safely and effectively. See full prescribing information for RUBY-FILL.
RUBY-FILL (rubidium Rb 82 generator)
To produce rubidium Rb 82 chloride injection, for intravenous use
Initial U.S. Approval: 1989

WARNING: HIGH LEVEL RADIATION EXPOSURE WITH USE OF INCORRECT ELUENT AND FAILURE TO FOLLOW QUALITY CONTROL TESTING PROCEDURE

Please see full prescribing information for complete boxed warning

High Level Radiation Exposure with Use of Incorrect Eluent

Using the incorrect eluent can cause high Strontium (Sr 82) and (Sr 85) breakthrough levels (5.1)

- Use only additive-free 0.9% Sodium Chloride Injection USP to elute the generator (2.5)
- Immediately stop the patient infusion and discontinue the use of the affected RUBY-FILL generator if the incorrect solution is used to elute the generator (4)
- Evaluate the patient’s radiation absorbed dose and monitor for the effects of radiation to critical organs such as bone marrow (2.9)

Excess Radiation Exposure with Failure to Follow the Quality Control Testing Procedure
Excess-radiation exposure occurs when the levels of Sr 82 or Sr 85 in the Rubidium Rb 82 Chloride injection exceed specific limits. (5.2)

- Strictly adhere to the generator quality control testing procedure (2.6)
- Stop using the generator if it reaches any of its Expiration Limit (2.7)

1 INDICATIONS AND USAGE

RUBY-FILL is a closed system used to produce rubidium Rb 82 chloride injection for intravenous use. Rubidium Rb 82 chloride injection is a radioactive diagnostic agent indicated for Positron Emission Tomography (PET) imaging of the myocardium under rest or pharmacologic stress conditions to evaluate regional myocardial perfusion in adult patients with suspected or existing coronary artery disease. (1)

2 DOSAGE AND ADMINISTRATION

Use RUBY-FILL with a specific Elution System. (2.4)

• Use only additive-free 0.9% Sodium Chloride Injection USP to elute the generator. (2.5)
• The recommended weight-based dose of rubidium Rb 82 is between 10 to 30 Megabecquerels (MBq)/kg [0.27 to 0.81 millicuries (mCi)/kg]. (2.2)
• Do not exceed a single dose of 2220 MBq (60 mCi) per rest or stress component of a procedure. (2.2)
• Administer the single dose at a rate of 15 to 30 mL/minute through a catheter inserted into a large peripheral vein; do not exceed an infusion volume of 60 mL. (2.2)
• Use the lowest dose necessary to obtain adequate cardiac visualization and individualize the dose depending on multiple factors, including, patient weight, imaging equipment and acquisition type used to perform the procedure. (2.2)
• Start imaging acquisition 60 to 90 seconds after completion of the infusion; if a longer circulation time is anticipated, wait for 120 seconds. Acquisition may be started immediately post-injection if dynamic imaging is needed. Image acquisition is typically 3 to 7 minutes long. (2.3)
• To obtain rest and stress images, wait 10 minutes after completion of the rest image acquisition then administer the pharmacologic stress agent in accordance with its prescribing information. After administration of the pharmacologic stress agent, infuse the second dose of Rb 82, at the time interval according to the prescribing information of the pharmacological stress agent and complete the stress image acquisition. (2.3)

3 DOSAGE FORMS AND STRENGTHS

RUBY-FILL consists of Sr 82 adsorbed on a hydrous stannic oxide column with an activity of 3145 to 4255 MBq (85 to 115 mCi) Sr 82 at calibration time. (3)

4 CONTRAINDICATIONS

RUBY-FILL is contraindicated if a solution other than additive-free 0.9% Sodium Chloride Injection USP has been used to elute the generator at any time. (4)

5 WARNINGS AND PRECAUTIONS

•Pharmacologic induction of cardiovascular stress: May be associated with serious adverse reactions such as myocardial infarction, arrhythmia, hypotension, bronchoconstriction, and cerebrovascular events. Perform testing only in setting where cardiac resuscitation equipment and trained staff are readily available. (5.3)

6 ADVERSE REACTIONS

To report SUSPECTED ADVERSE REACTIONS, contact Jubilant DraxImage Inc., dba Jubilant RadiopharmaTM at 1-888-633-5343 or FDA at 1-800-FDA-1088 or www.fda.gov/medwatch.

8 USE IN SPECIFIC POPULATIONS

• Lactation: Do not resume breastfeeding until at least one hour after completion of RUBY-FILL infusion. (8.2)

FULL PRESCRIBING INFORMATION

WARNING: HIGH LEVEL RADIATION EXPOSURE WITH USE OF INCORRECT ELUENT AND FAILURE TO FOLLOW QUALITY CONTROL TESTING PROCEDURE

High Level Radiation Exposure with Use of Incorrect Eluent

Patients are exposed to high radiation levels when the generator is eluted with the incorrect eluent due to high Sr 82 and Sr 85 breakthrough levels [see Warnings and Precautions (5.1)]

- Use only additive-free 0.9% Sodium Chloride Injection USP to elute the generator [see Dosage and Administration (2.5)]
- Immediately stop the patient infusion and discontinue the use of the affected RUBY-FILL (Rb 82) generator, if the incorrect solution is used to elute the generator [see Contraindications (4)].
- Evaluate the patient’s radiation absorbed dose and monitor for the effects of radiation to critical organs such as bone marrow [(see Dosage and Administration (2.9)].

Excess Radiation Exposure with Failure to Follow Quality Control Testing Procedure

Excess radiation exposure occurs when the levels of Sr 82 or Sr 85 in the rubidium Rb 82 chloride injection exceed specified limits [see Warnings and Precautions (5.2)].

- The system automatically generates a record and saves the data for each generator eluate volume, including flushing and test volumes. Total cumulative eluate volumes are also recorded and saved for the life of the generator [see Dosage and Administration (2.5)].
- Strictly adhere to the generator quality control testing procedure, to minimize the risk of excess radiation exposure, including daily testing and additional testing at Alert Limits [see Dosage and Administration (2.6)]
- Stop use of a generator at any of the following Expiration Limits. Expiry Limits are:
  - o 30 L for the generator's cumulative eluate volume, or
  - o Expiration date of the generator (60 days post-calibration)
  - o An eluate Sr 82 level of 0.01 mcCi /mCi (kBq/MBq) Rb 82, or
  - o An eluate Sr 85 level of 0.1 mcCi /mCi (kBq/MBq) Rb 82 [see Dosage and Administration (2.7)].

1 INDICATIONS AND USAGE

RUBY-FILL is a closed system used to produce rubidium Rb 82 chloride injection for intravenous administration. Rubidium Rb 82 chloride injection is indicated for Positron Emission Tomography (PET) imaging of the myocardium under rest or pharmacologic stress conditions to evaluate regional myocardial perfusion in adult patients with suspected or existing coronary artery disease.

2 DOSAGE AND ADMINISTRATION

2.1 Radiation Safety - Drug Handling

Rubidium Rb 82 is a radioactive drug and should be handled with appropriate safety measures to minimize radiation exposure during administration [see Warnings and Precautions (5.3]).

- Use only additive-free 0.9% Sodium Chloride Injection USP to elute the generator [see Boxed Warning, Contraindications (4), Warnings and Precautions (5.1)].
- Use waterproof gloves and effective shielding when handling rubidium Rb 82 chloride injection and the RUBY Rubidium Elution System.
- Use aseptic techniques in all drug handling.
- Visually inspect the drug for particulate matter and discoloration prior to administration whenever solution and container permit. Do not administer eluate from the generator if there is any evidence of foreign matter.

2.2 Recommended Dose and Administration Instructions

- The recommended weight-based dose of rubidium Rb 82 chloride to be administered per rest or stress component of a PET myocardial perfusion imaging (MPI) procedure is between 10 to 30 Megabecquerels (MBq)/kg [0.27 to 0.81 millicuries (mCi)/kg].
- Do not exceed a single dose of 2220 MBq (60 mCi).
- Use the lowest dose necessary to obtain adequate cardiac visualization and individualize the weight-based dose depending on multiple factors, including, patient weight, imaging equipment and acquisition type used to perform the procedure. For example, 3D imaging acquisition may require doses at the lower end of the recommended range compared to 2D imaging.
- Administer the single dose at a rate of 15 to 30 mL/minute through a catheter inserted into a large peripheral vein; do not exceed an infusion volume of 60 mL.
- Instruct patients to void as soon as a study is completed and as often as possible thereafter for at least one hour.
- The maximum available activity (delivery limit) will decrease as the generator ages [see Dosage and Administration (2.8)].

2.3 Image Acquisition Guidelines

For Rest Imaging:

- Administer a single (“rest”) rubidium Rb 82 chloride dose;
- Start imaging 60 to 90 seconds after completion of the infusion of the rest dose and acquire images for 3 to 7 minutes.

For Stress Imaging:

- Begin the study 10 minutes after completion of the resting dose infusion, to allow for sufficient Rb 82 decay;
- Administer a pharmacologic stress agent in accordance with its prescribing information;
- After administration of the pharmacologic stress agent, administer the second dose of Rb 82 at the time interval according to the prescribing information of the pharmacological stress agent;
- Start imaging 60 to 90 seconds after completion of the stress rubidium Rb 82 chloride dose infusion and acquire images for 3 to 7 minutes.

For Both Rest and Stress Imaging:

- If a longer circulation time is anticipated (e.g., in a patient with severe left ventricular dysfunction), start imaging 120 seconds after the rest dose.
- Acquisition may be started immediately post-injection if dynamic imaging is needed.

2.4 Elution System

- Use RUBY-FILL Rubidium Rb 82 Generator only with an elution system specifically designed for use with the generator (RUBY Rubidium Elution System) and capable of accurate measurement and delivery of doses of rubidium Rb 82 chloride injection.
- The generator used with the elution system provides ± 10% accuracy for rubidium Rb 82 chloride doses between 370 to 2220 MBq (10 to 60 mCi)
- Follow instructions in the RUBY Rubidium Elution System User Manual for the set up and intravenous infusion of rubidium Rb 82 chloride injection dose.

2.5 Directions for Eluting Rubidium Rb 82 Chloride Injection

- Use only additive-free 0.9 % Sodium Chloride Injection USP to elute the generator [see Boxed Warning, Contraindications (4) and Warnings and Precautions (5.1)].
- Prepare the 0.9% Sodium Chloride Injection USP for use with the Saline Confirmation Label
  - Affix the saline confirmation label provided with the RUBY Rubidium Elution System on the clear side of the additive-free 0.9% Sodium Chloride Injection USP bag and install on the RUBY Rubidium Elution System.
  - Prepare the intravenous administration port in accordance with the DOSAGE AND ADMINISTRATION section of the approved prescribing information of the 0.9% Sodium Chloride Injection USP.
  - The port of the sodium chloride bag must be penetrated only one time.
  - Once the bag port is penetrated, it should remain installed on the RUBY Rubidium Elution System for its entire period of use. A maximum use time of 12 hours from the initial port penetration is permitted.
  - Before the next patient, replace the saline bag as part of the mandatory daily quality control procedure.
- Allow at least 10 minutes between elutions for regeneration of Rb 82.
- The system will automatically discard the first 75 mL eluate each day the generator is first eluted.
- The RUBY Rubidium Elution System automatically generates records and saves data of all eluate volumes (from flushing, QC testing, patient infusions), representing the cumulative volume of eluate from the generator.

2.6 Quality Control Testing Procedure

- Elute with additive-free 0.9% Sodium Chloride Injection USP only. [see Boxed Warning, Contraindications (4) and Warnings and Precautions (5.1)].
- Replace the saline bag daily as part of the mandatory daily quality control procedure.
- Use the ionization chamber-type dose calibrator with the elution system (used specifically with the RUBY-FILL Rubidium Rb 82 Generator) for eluate testing.
- Perform Mandatory Eluate Testing (i.e. Quality Control Testing Procedure) to determine Rb 82, Sr 82, and Sr 85 levels:
  1. Daily - Before administering rubidium Rb 82 chloride injection to the first patient each day.
  2. Repeat Every 4 patients after an Alert Limit has been detected.
    Alert Limits:
    - 20 L total elution volume has passed through the generator column, or
    - Sr 82 level reaches 0.004 mcCi per mCi (kBq per MBq) Rb 82, or
    - Sr 85 level reaches 0.04 mcCi per mCi (kBq per MBq) Rb 82.
  3. Immediately after detection of the volume alert limit (20 L).

- The elution system will automatically indicate when alert limits have been reached and require that additional tests be performed.

When the Quality Control Testing Procedure is performed as described in the User Manual, the system automatically performs the following eluate testing:

Rubidium Eluate Testing:

1. The dose calibrator is automatically set for Rb 82 within the Elution System.
2. The Quality Control test begins by automatically initiating a generator flush using 75 mL of 0.9% Sodium Chloride Injection USP. This eluate is by default diverted towards the waste container and is ultimately discarded.
3. After the generator flush, the system waits approximately 15.2 minutes to accomplish a complete generator recharge of 12 Rb 82 half-lives
4. The system then elutes a calibration sample (35 mL of 0.9% Sodium Chloride Injection USP at 20 mL/min). Using the dose calibrator, the system automatically quantifies the activity of Rb 82 in the calibration sample (Rb 82 decay does not need to be corrected for because of a real-time automated measurement).

Strontium Eluate Testing (Strontium Breakthrough):

1. Using the calibration sample obtained from the Rb 82 eluate testing, the system allows the sample to stand for 30 minutes to allow for the complete decay of Rb 82.
2. The system measures the activity of the sample to automatically determine the total Sr 82 and Sr 85 activity.
3. The system automatically determines the ratio (R) on the day (post calibration) of the measurement using the ratio of Sr 85/Sr 82 on the day of calibration provided on the generator label and the Sr 85/Sr 82 ratio factor from the Sr 85/Sr 82 ratio based on generator age using the following equation:

4. The system uses a correction factor (F) of 0.48 to compensate for the contribution of Sr 85 to the reading.

5. The system calculates the amount of Sr 82 in the sample using the following equation:

6. The system determines if Sr 82 in the eluate exceeds an Alert or Expiration Limit by dividing the mcCi (or kBq) of Sr 82 by the mCi (or MBq) of Rb 82 at End of Elution (see below for further instructions based on the Sr 82 level)

7. The system determines if Sr 85 in the eluate exceeds an Alert or Expiration Limit by multiplying the result obtained in step 6 by (R) as calculated in step 3 (above).

The system uses Table 1 to calculate the decay factor for Rb 82

TABLE 1
Physical Decay Chart: Rb 82 half-life 75 seconds
Seconds | Fraction Remaining | Seconds | Fraction Remaining
0* | 1.00 | 165 | 0.218
15 | 0.871 | 180 | 0.190
30 | 0.758 | 195 | 0.165
45 | 0.660 | 210 | 0.144
60 | 0.574 | 225 | 0.125
75 | 0.500 | 240 | 0.109
90 | 0.435 | 255 | 0.095
105 | 0.379 | 270 | 0.083
120 | 0.330 | 285 | 0.072
135 | 0.287 | 300 | 0.063
150 | 0.250

*Elution time

The system uses Table 2 to calculate the ratio (R) of Sr 85/Sr 82.

TABLE 2
Sr 85/Sr 82 Ratio Chart (Sr 85 T1/2 = 65 days, Sr 82 T1/2 = 25 days)
Days | RatioFactor | Days | Ratio Factor | Days | Ratio Factor
0* | 1.00 | 21 | 1.43 | 42 | 2.05
1 | 1.02 | 22 | 1.46 | 43 | 2.08
2 | 1.03 | 23 | 1.48 | 44 | 2.12
3 | 1.05 | 24 | 1.51 | 45 | 2.15
4 | 1.07 | 25 | 1.53 | 46 | 2.19
5 | 1.09 | 26 | 1.56 | 47 | 2.23
6 | 1.11 | 27 | 1.58 | 48 | 2.27
7 | 1.13 | 28 | 1.61 | 49 | 2.30
8 | 1.15 | 29 | 1.64 | 50 | 2.34
9 | 1.17 | 30 | 1.67 | 51 | 2.38
10 | 1.19 | 31 | 1.70 | 52 | 2.43
11 | 1.21 | 32 | 1.73 | 53 | 2.47
12 | 1.23 | 33 | 1.76 | 54 | 2.51
13 | 1.25 | 34 | 1.79 | 55 | 2.55
14 | 1.27 | 35 | 1.82 | 56 | 2.60
15 | 1.29 | 36 | 1.85 | 57 | 2.64
16 | 1.31 | 37 | 1.88 | 58 | 2.69
17 | 1.34 | 38 | 1.91 | 59 | 2.73
18 | 1.36 | 39 | 1.95 | 60 | 2.78
19 | 1.38 | 40 | 1.98
20 | 1.41 | 41 | 2.01

* Day of Calibration.

2.7 RUBY-FILL Expiration

Stop use of the RUBY-FILL Rubidium Rb 82 Generator once any one of the following Expiration Limits is reached:

- A total elution volume of 30 L has passed through the generator column, or
- Expiration date of the generator (60 days post-calibration), or
- An eluate Sr 82 level of 0.01 mcCi/mCi (kBq/MBq) Rb 82, or
- An eluate Sr 85 level of 0.1 mcCi/mCi (kBq/MBq) Rb 82.

2.8 RUBY-FILL Dose Delivery Limit

The maximum available activity (delivery limit) will decrease as the generator ages. Certain doses, including the maximum recommended dose [60 mCi (2220 MBq)], are not achievable for the entire shelf-life of the generator. Table 3 provides an estimate of the maximum available activity of Rubidium Rb 82 (Delivery Limit) as a function of generator age.

TABLE 3 Rubidium Rb 82 Dose Delivery Limit Based on Generator Age^1
Generator Age (days) ^2 | Maximum Rubidium Dose; (Delivery Limit)
0 to 17 | 60 mCi (2220 MBq)
24 | 50 mCi (1850 MBq)
32 | 40 mCi (1480 MBq)
42 | 30 mCi (1110 MBq)
57 | 20 mCi (740 MBq)

^1Estimate is based on a 100 mCi (3700 MBq) Sr 82 generator at calibration.

^2Generator age at which delivery limit is reached varies with generator activity at release. For example, an 85 mCi (3145 MBq) generator and a 115 mCi (4255 MBq) generator will reach a delivery limit < 60 mCi at ≥ 12 days and ≥ 23 days, respectively.

2.9 Radiation Dosimetry

The estimated radiation absorbed dose coefficients for Rb 82, Sr 82, and Sr 85 from an intravenous injection of rubidium Rb 82 chloride are shown in Table 4.

TABLE 4
Adult absorbed dose per radioisotope activity associated with injection
Organ | ^82 Rb^1; (mcGy/MBq) | ^82 Sr^2; (mcGy/kBq) | ^85 Sr^2; (mcGy/kBq)
Adrenals | 2.4 | 2.9 | 1.4
Bone surfaces | 0.42 | 29 | 2.7
Brain | 0.14 | 2.2 | 0.8
Breast | 0.19 | 1.9 | 0.5
Gallbladder wall | 0.72 | 2.3 | 0.8
Gastrointestinal tract
Esophagus^3 | 1.5 | 2.1 | 0.6
Stomach wall | 0.83 | 2.1 | 0.6
Small intestine wall | 2.0 | 2.6 | 1.1
Colon wall | 1.1 | 9.7 | 1.2
(ULI wall) | 1.1 | 6.4 | 1.0
(LLI wall) | 1.1 | 14 | 1.4
Heart wall | 4.0 | 2.2 | 0.7
Kidneys | 9.3 | 2.5 | 0.7
Liver | 1.0 | 2.2 | 0.7
Lungs | 2.6 | 2.2 | 0.8
Muscles | 0.23 | 2.2 | 0.7
Ovaries | 0.50 | 2.8 | 1.2
Pancreas | 2.6 | 2.5 | 0.9
Red marrow | 0.38 | 25 | 2.7
Skin | 0.18 | 1.9 | 0.5
Spleen | 0.18 | 2.2 | 0.7
Testes | 0.26 | 2.0 | 0.5
Thymus | 1.5 | 2.1 | 0.6
Thyroid | 0.31 | 2.2 | 0.7
Urinary bladder wall | 0.18 | 5.9 | 0.8
Uterus | 1.0 | 2.5 | 0.9
Remaining organs | 0.31 | - | -
Effective dose per unit activity | 1.1 mcSv/MBq | 6.3 mcSv/kBq | 1.1 mcSv/kBq
^1 Rb 82 doses are averages of rest and stress dosimetry data. To calculate organ doses (mcGy) from Rb 82, multiply the dose coefficient for each organ by the administered activity in MBq.
^2 To calculate organ doses attributable to Sr 82 and Sr 85, multiply those dose coefficients by the respective strontium activities associated with the injection.
^3The absorbed dose to the thymus is used as a substitute.

3 DOSAGE FORMS AND STRENGTHS

RUBY-FILL is a closed system used to produce rubidium Rb 82 chloride injection for intravenous use. RUBY-FILL consists of Sr 82 adsorbed on a hydrous stannic oxide column with an activity of 3145 to 4255 MBq (85 to 115 mCi) Sr 82 at calibration time.

4 CONTRAINDICATIONS

RUBY-FILL is contraindicated for use if a solution other than additive-free 0.9% Sodium Chloride Injection USP has been used to elute the generator at any time. Immediately stop the patient infusion and permanently discontinue the use of the affected RUBY-FILL generator whenever the incorrect eluent is used [see Boxed Warning, Contraindications (4), Warnings and Precautions (5.1)].

5 WARNINGS AND PRECAUTIONS

5.1 High Level Radiation Exposure with Use of Incorrect Eluent

Use only additive-free 0.9% Sodium Chloride Injection USP to elute the generator. Apply the provided saline confirmation label to the additive-free 0.9% Sodium Chloride Injection USP bag before use. Additives present in other solutions (particularly calcium ions) expose patients to high levels of radiation by causing the release of large amounts of Sr 82 and Sr 85 into the eluate regardless of the generator’s age or prior use [Dosage and Administration (2.1, 2.5, 2.6)].

Immediately stop the patient infusion and discontinue use of the affected RUBY-FILL generator if the incorrect eluent is used and evaluate the patient’s radiation absorbed dose and monitor for the effects of radiation to critical organs such as bone marrow. When solutions containing calcium ions are used to elute the generator, high levels of radioactivity are present in the eluate, even with the subsequent use of additive-free 0.9% Sodium Chloride Injection USP [see Boxed Warning, Dosage and Administration (2.9), and Contraindications (4)].

5.2 Excess Radiation Exposure with Failure to Follow the Quality Control Testing Procedure

Excess radiation exposure occurs when the Sr 82 and Sr 85 levels in rubidium Rb 82 chloride injections exceed the specified generator eluate limits. Strictly adhere to the quality control testing procedure to minimize radiation exposure to the patient. Stop using the rubidium generator when the expiration limits are reached [see Dosage and Administration (2.6) and (2.7)].

5.3 Risks Associated with Pharmacologic Stress

Pharmacologic induction of cardiovascular stress may be associated with serious adverse reactions such as myocardial infarction, arrhythmia, hypotension, bronchoconstriction, and cerebrovascular events. Perform pharmacologic stress testing in accordance with the pharmacologic stress agent’s prescribing information and only in the setting where cardiac resuscitation equipment and trained staff are readily available.

5.4 Radiation Risks

RUBY-FILL use contributes to a patient’s overall long-term cumulative radiation exposure. Long-term cumulative radiation exposure is associated with an increased risk for cancer. Ensure safe handling to minimize radiation exposure to the patient and health care providers. Encourage patients to void as soon as a study is completed and as often as possible thereafter for at least one hour [see Dosage and Administration (2.1) and (2.2)].

6 ADVERSE REACTIONS

The following serious adverse reaction associated with the use of rubidium Rb 82 chloride was identified in clinical trials or post marketing reports. Because these reactions are reported voluntarily from a population of uncertain size, it is not always possible to reliably estimate their frequency or establish a causal relationship to drug exposure.

Radiation Exposure
High level radiation exposure to the bone marrow has occurred in some patients due to Sr 82 and Sr 85 breakthrough in the eluate when an incorrect solution was used to elute the rubidium Rb 82 generator [see Boxed Warning, Warnings and Precautions (5.1)]. Excess radiation exposure has occurred in some patients who received rubidium Rb 82 chloride injection at clinical sites where generator eluate testing appeared insufficient [see Boxed Warning, Warnings and Precautions (5.2), Dosage and Administration (2.6)].

8 USE IN SPECIFIC POPULATIONS

8.1 Pregnancy

Risk Summary
There are no data available on the use of rubidium Rb 82 in pregnant women. Animal reproduction studies with rubidium Rb 82 chloride have not been conducted. However, all radiopharmaceuticals have the potential to cause fetal harm depending on the fetal stage of development and the magnitude of the radiation dose. If considering rubidium Rb 82 chloride injection administration to a pregnant woman, inform the patient about the potential for adverse pregnancy outcomes based on the radiation dose from Rb 82 and the gestational timing of exposure.

The estimated background risk of major birth defects and miscarriage for the indicated population is unknown. In the U.S. general population, the estimated background risk of major birth defects and miscarriage in clinically recognized pregnancies is 2 to 4% and 15 to 20%, respectively.

8.2 Lactation

Risk Summary
There is no information regarding the presence of Rb 82 chloride in human milk, the effects on the breastfed infant or the effects on milk production. Due to the short half-life of Rb 82 chloride (75 seconds), exposure of a breast fed infant through breast milk can be minimized by temporary discontinuation of breastfeeding [See Clinical Considerations]. The developmental and health benefits of breastfeeding should be considered along with the mother’s clinical need for Rb 82, any potential adverse effects on the breastfed child from Rb 82 or from the underlying maternal condition.

Clinical Considerations
Minimizing Exposure
Exposure to Rb 82 chloride through breast milk can be minimized if breastfeeding is discontinued when Rb 82 chloride injection is administered. Do not resume breastfeeding until at least one hour after completion of RUBY-FILL infusion.

8.4 Pediatric Use

The safety and effectiveness of rubidium Rb 82 chloride injection in pediatric patients have not been established.

8.5 Geriatric Use

In elderly patients with a clinically important decrease in cardiac function, lengthen the delay between infusion and image acquisition [see Dosage and Administration (2.3)]. Observe for the possibility of fluid overload from the infusion.

11 DESCRIPTION

11.1 Chemical Characteristics

RUBY-FILL Rubidium Rb 82 Generator contains accelerator-produced Sr 82 adsorbed on stannic oxide in a lead-shielded column and provides a means for obtaining sterile non-pyrogenic solutions of rubidium Rb 82 chloride injection. The chemical form of Rb 82 is ^82RbCl.

The amount (mCi) of Rb 82 obtained in each elution will depend on the potency of the generator. When used with the RUBY Rubidium Elution System, the generator provides ± 10% accuracy for rubidium Rb 82 chloride doses between 370 to 2220 MBq (10 to 60 mCi).

When eluted at a rate of 15 to 30 mL/minute, each generator eluate at the end of elution should not contain more than 0.02 mcCi (0.74 kBq) of Sr 82 and not more than 0.2 mcCi (7.4 kBq) of Sr 85 per mCi of rubidium Rb 82 chloride injection, and not more than 1 mcg of tin per mL of eluate.

11.2 Physical Characteristics

Rb 82 decays by positron emission and associated gamma emission with a physical half-life of 75 seconds. Table 5 shows the annihilation photons released following positron emission which are useful for detection and imaging studies.

The decay modes of Rb 82 are: 95.5% by positron emission, resulting in the production of annihilation radiation, i.e., two 511 keV gamma rays; and 4.5% by electron capture, resulting in the emission of “prompt” gamma rays of predominantly 776.5 keV. Both decay modes lead directly to the formation of stable Kr 82.

TABLE 5
Principal Radiation Emission Data
Radiation | Mean Percent Per Disintegration | Mean Energy (keV)
Annihilation photons (2) | 191.01 | 511 (each)
Gamma rays | 13 to 15 | 776.5

The specific gamma ray constant for Rb 82 is 6.33 R cm^2 / mCi h (1.23 × 10^-12 C m^2 / kg MBq s). The first half-value layer is 0.53 cm of lead (Pb). Table 6 shows a range of values for the relative attenuation of the radiation emitted by this radionuclide that results from interposition of various thicknesses of Pb. For example, the use of a 6.15 cm thickness of Pb will attenuate the radiation emitted by a factor of about 1,000.

TABLE 6
Radiation Attenuation by Lead Shielding
Shield Thickness (Pb) cm | Attenuation Factor
0.53 | 0.5
1.68 | 10^-1
3.55 | 10^-2
6.15 | 10^-3
9.3 | 10^-4

Sr 82 (half-life of 25 days; 600 hrs.) decays to Rb 82. To correct for physical decay of Sr 82, Table 7 shows the fractions that remain at selected intervals after the time of calibration.

TABLE 7
Physical Decay Chart: Sr 82 half-life 25 days
Days | Fraction Remaining | Days | Fraction Remaining | Days | Fraction Remaining
0* | 1.000 | 21 | 0.559 | 41 | 0.321
1 | 0.973 | 22 | 0.543 | 42 | 0.312
2 | 0.946 | 23 | 0.529 | 43 | 0.304
3 | 0.920 | 24 | 0.514 | 44 | 0.295
4 | 0.895 | 25 | 0.500 | 45 | 0.287
5 | 0.871 | 26 | 0.486 | 46 | 0.279
6 | 0.847 | 27 | 0.473 | 47 | 0.272
7 | 0.824 | 28 | 0.460 | 48 | 0.264
8 | 0.801 | 29 | 0.448 | 49 | 0.257
9 | 0.779 | 30 | 0.435 | 50 | 0.250
10 | 0.758 | 31 | 0.423 | 51 | 0.243
11 | 0.737 | 32 | 0.412 | 52 | 0.237
12 | 0.717 | 33 | 0.401 | 53 | 0.230
13 | 0.697 | 34 | 0.390 | 54 | 0.224
14 | 0.678 | 35 | 0.379 | 55 | 0.218
15 | 0.660 | 36 | 0.369 | 56 | 0.212
16 | 0.642 | 37 | 0.358 | 57 | 0.206
17 | 0.624 | 38 | 0.349 | 58 | 0.200
18 | 0.607 | 39 | 0.339 | 59 | 0.195
19 | 0.591 | 40 | 0.330 | 60 | 0.189
20 | 0.574

* Calibration time

To correct for physical decay of Rb 82, Table 1 shows the fraction of Rb 82 remaining in all 15 second intervals up to 300 seconds after time of calibration [see Dosage and Administration (2.6)].

12 CLINICAL PHARMACOLOGY

12.1 Mechanism of Action

Rb 82 is analogous to potassium ion (K^+) in its biochemical behavior and is rapidly extracted by the myocardium proportional to the blood flow. Rb^+ participates in the sodium-potassium (Na^+/K^+) ion exchange pumps that are present in cell membranes. The intracellular uptake of Rb 82 requires maintenance of ionic gradient across cell membranes. Rb 82 radioactivity in viable myocardium is higher than in infarcted tissue, reflecting intracellular retention.

12.2 Pharmacodynamics

In human studies, myocardial activity was noted within the first minute after peripheral intravenous injection of Rb 82. When areas of infarction or ischemia are present in the myocardium, they are visualized within 2 to 7 minutes after injection as photon-deficient, or “cold”, areas on the myocardial perfusion scan. In patients with reduced cardiac function, transit of the injected dose from the peripheral infusion site to the myocardium may be delayed.

Blood flow brings Rb 82 to all areas of the body during the first pass of circulation. Accordingly, visible uptake is observed in highly vascularized organs, such as the kidneys, liver, spleen and lungs.

12.3 Pharmacokinetics

With a physical half-life of 75 seconds, Rb 82 is converted by radioactive decay into stable Kr 82 gas, which is passively expired by the lungs.

13 NONCLINICAL TOXICOLOGY

13.1 Carcinogenesis, Mutagenesis, Impairment of Fertility

No long-term studies have been performed to evaluate carcinogenic potential, mutagenicity potential, or to determine whether rubidium Rb 82 chloride injection may affect fertility in males or females.

14 CLINICAL STUDIES

In a descriptive, prospective, blinded image interpretation study of adult patients with known or suspected coronary artery disease, myocardial perfusion deficits in stress and rest PET images obtained with ammonia N 13 (n = 111) or Rb 82 (n = 82) were compared to changes in stenosis flow reserve (SFR) as determined by coronary angiography. PET perfusion defects at rest and stress for seven cardiac regions (anterior, apical, anteroseptal, posteroseptal, anterolateral, posterolateral, and inferior walls) were graded on a scale of 0 (normal) to 5 (severe). Values for stenosis flow reserve, defined as flow at maximum coronary vasodilatation relative to rest flow, ranged from 0 (total occlusion) to 5 (normal). With increasing impairment of flow reserve, the subjective PET defect severity increased. A PET defect score of 2 or higher was positively correlated with flow reserve impairment (SFR < 3).

A systematic review of published literature was conducted using pre-defined inclusion/exclusion criteria which resulted in identification of 10 studies evaluating the use of Rb 82 PET myocardial perfusion imaging (MPI) for the identification of coronary artery disease as defined by catheter-based angiography. In these studies, the patient was the unit of analysis and 50% stenosis was the threshold for clinically significant coronary artery disease (CAD). Of these 10 studies, 9 studies were included in a meta-analysis for sensitivity (excluding one study with 100% sensitivity) and 7 studies were included in a meta-analysis of specificity (excluding 3 studies with 100% specificity). A random effects model yielded overall estimates of sensitivity and specificity of 92% (95% CI: 89% to 95%) and 81% (95% CI: 76% to 86%), respectively. The use of meta-analysis in establishing performance characteristics is limited, particularly by the possibility of publication bias (positive results being more likely to be published than negative results) which is difficult to detect especially when based on a limited number of small studies.

16 HOW SUPPLIED/STORAGE AND HANDLING

16.1 How Supplied

RUBY-FILL Rubidium Rb 82 Generator consists of Sr 82 adsorbed on a hydrous stannic oxide column with an activity of 3145 to 4255 MBq (85 to 115 mCi) Sr 82 at calibration time. A lead shield encases the generator. The container label provides complete assay data for each generator. Use RUBY-FILL Rubidium Rb 82 Generator only with an appropriate, properly calibrated Elution System (RUBY Rubidium Elution System) labeled for use with the generator.

16.2 Storage and Handling

- Store the generator at 20 to 25 ºC (68 to 77 ºF).
- Receipt, transfer, possession, storage, disposal or use of this product is subject to the radioactive material regulations and licensing requirements of the U.S. Nuclear Regulatory Commission (NRC), Agreement States or Licensing States as appropriate. Do not dispose of the generator in regular refuse systems.
- For questions about the disposal of the RUBY-FILL Rubidium Rb 82 Generator, contact Jubilant Radiopharma at 1-888-633-5343.

17 PATIENT COUNSELING INFORMATION

Pregnancy
Advise a pregnant woman of the potential risk to a fetus.

Lactation
Advise lactating women that exposure to Rb 82 chloride through breast milk can be minimized if breastfeeding is discontinued when Rb 82 chloride injection is administered. Advise lactating women not to resume breastfeeding for at least one hour after completion of rubidium Rb 82 infusion.

General Safety Precautions
Advise patients to void after completion of each image acquisition session and as often as possible for one hour after completion of the PET scan.

Manufactured by:

Jubilant DraxImage Inc., dba Jubilant RadiopharmaTM
16 751 TransCanada Highway
Kirkland, Quebec H9H 4J4 Canada
1-888-633-5343
www.jubilantradiopharma.com

Version: 5.1

Jubilant RadiopharmaTM is a trademark used under license by Jubilant DraxImage Inc.

PACKAGE LABEL.PRINCIPAL DISPLAY PANEL

RUBY FILL RUBIDIUM Rb 82 GENERATOR - MAIN LABEL

100mCi

Generator column contains Strontium Sr 82 adsorbed on hydrous stannic oxide.

Store the generator at 20-25 ºC (68-77 ºF).

Rx only

RUBY FILL RUBIDIUM Rb 82 GENERATOR - IDENTIFICATION

RUBY FILL RUBIDIUM RB 82 GENERATOR - ASSAY LABEL